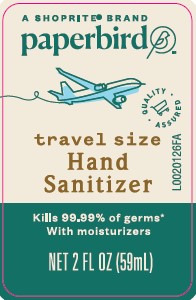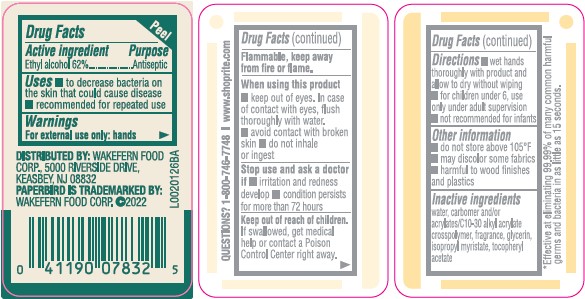 DRUG LABEL: Alcohol
NDC: 41190-849 | Form: LIQUID
Manufacturer: Wakefern Food Corp.
Category: otc | Type: HUMAN OTC DRUG LABEL
Date: 20260213

ACTIVE INGREDIENTS: ALCOHOL 62 mg/1 mL
INACTIVE INGREDIENTS: WATER; CARBOMER INTERPOLYMER TYPE A (ALLYL SUCROSE CROSSLINKED); GLYCERIN; ISOPROPYL MYRISTATE; TOCOPHEROL

Paperbird 849.001/849AB-BA
Moisturizing Hand Sanitizer

Active ingredient

Ethyl Alcohol 62%

Purpose

Antiseptic

Uses

- to decrease bacteria on the skin that could cause disease
- recommended for repeated use

Warnings

For external use only-hands

Flammable, keep away from fire or flame.

When using this product

- keep out of eyes. In case of contact with eyes, flush thoroughly with water.
- avoid contact with broken skin
- do not inhale or ingest

Stop use and ask a doctor if

- irritation and redness develop
- condition persists for more than 72 hours

Keep out of reach of children.

If swallowed, get medical help or contact a Poison Control Center right away.

Directions

- wet hands thoroughly with product and allow to dry without wiping
- for children under 6, use only under adult supervision
- not recommended for infants

Other information

- do not store above 105⁰F
- may discolor some fabrics
- harmful to wood finishes and plastics

Inactive ingredients

water, carbomer and/or acrylates/C10-30 alkyl acrylate crosspolymer, fragrance, glycerin, isopropyl myristate, tocopheryl acetate

Claims

*Effective at eliminating 99.99% of many common harmful germs and bacteria in as little as 15 seconds.

ADVERSE REACTION

DISTRIBUTED BY: WAKEFERN FOOD CORP., 5000 RIVERSIDE DRIVE,

KEASBEY, NJ 08832

PAPERBIRD IS A TRADEMARKED BY: WAKEFERN COOD CORP. 2022

PRINCIPAL DISPLAY PANEL

A SHOPRITE®BRAND

paperbird™

QUALITY ASSURED

travel size

Hand Sanitizer

Kills 99.99% of germs*

With moisturizers

NET 2 FL OZ (59 mL)